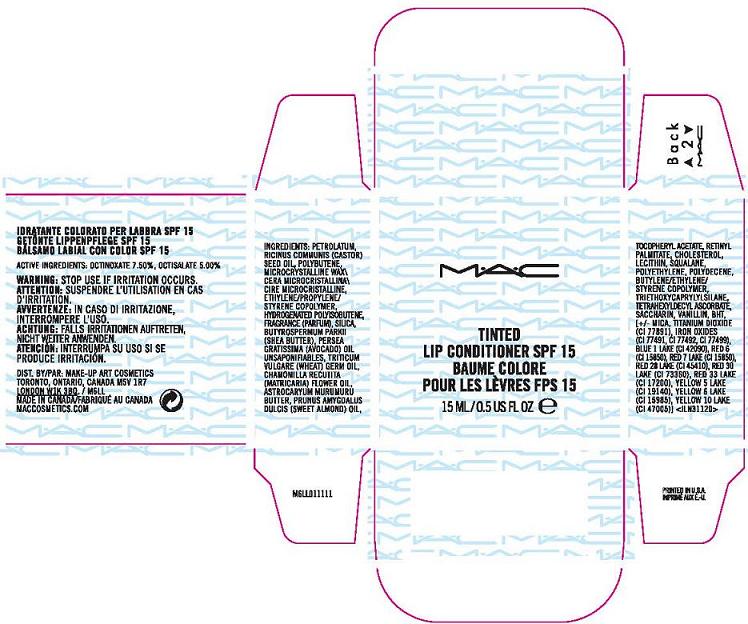 DRUG LABEL: TINTED LIP CONDITIONER
NDC: 40046-0051 | Form: GEL
Manufacturer: MAKEUP ART COSMETICS
Category: otc | Type: HUMAN OTC DRUG LABEL
Date: 20110825

ACTIVE INGREDIENTS: OCTINOXATE 7.5 mL/100 mL; OCTISALATE 5.0 mL/100 mL
INACTIVE INGREDIENTS: PETROLATUM; CASTOR OIL; MICROCRYSTALLINE WAX; SILICON DIOXIDE               ; POLYISOBUTYLENE (35000 MW); LECITHIN, SOYBEAN; ALMOND OIL; SHEA BUTTER; ASTROCARYUM MURUMURU SEED BUTTER; CHOLESTEROL; WHEAT GERM OIL; HIGH DENSITY POLYETHYLENE; TRIETHOXYCAPRYLYLSILANE; STANNIC OXIDE                    ; SACCHARIN; BUTYLATED HYDROXYTOLUENE; D&C RED NO. 6; D&C RED NO. 7; D&C RED NO. 28; D&C RED NO. 30; D&C RED NO. 33; FD&C YELLOW NO. 5; FD&C YELLOW NO. 6; FERRIC OXIDE RED; FERRIC OXIDE YELLOW; FERROSOFERRIC OXIDE

ACTIVE INGREDIENTS: OCTINOXATE 7.50% [] OCTISALATE 5.00%

INACTIVE INGREDIENT

INACTIVE INGREDIENTS: PETROLATUM [] RICINUS COMMUNIS (CASTOR) SEED OIL [] POLYBUTENE [] MICROCRYSTALLINE WAX \CERA MICROCRISTALLINA\CIRE MICROCRISTALLINE [] ETHYLENE/PROPYLENE/STYRENE COPOLYMER [] HYDROGENATED POLYISOBUTENE [] FRAGRANCE (PARFUM) [] SILICA [] BUTYROSPERMUM PARKII (SHEA BUTTER) [] PERSEA GRATISSIMA (AVOCADO) OIL UNSAPONIFIABLES [] TRITICUM VULGARE (WHEAT) GERM OIL [] CHAMOMILLA RECUTITA (MATRICARIA) FLOWER OIL [] ASTROCARYUM MURUMURU BUTTER [] PRUNUS AMYGDALUS DULCIS (SWEET ALMOND) OIL [] TOCOPHERYL ACETATE [] RETINYL PALMITATE [] CHOLESTEROL [] LECITHIN [] SQUALANE [] POLYETHYLENE [] POLYDECENE [] BUTYLENE/ETHYLENE/STYRENE COPOLYMER [] TRIETHOXYCAPRYLYLSILANE [] TETRAHEXYLDECYL ASCORBATE [] SACCHARIN [] VANILLIN [] BHT [] [+/- MICA [] TITANIUM DIOXIDE (CI 77891) [] IRON OXIDES (CI 77491, CI 77492, CI 77499) [] BLUE 1 LAKE (CI 42090) [] RED 6 (CI 15850) [] RED 7 LAKE (CI 15850) [] RED 28 LAKE (CI 45410) [] RED 30 LAKE (CI 73360) [] RED 33 LAKE (CI 17200) [] YELLOW 5 LAKE (CI 19140) [] YELLOW 6 LAKE (CI 15985) [] YELLOW 10 LAKE (CI 47005)

WARNINGS

WARNING: STOP USE IF IRRITATION OCCURS.

PACKAGE LABEL

PRINCIPAL DISPLAY PANEL:

MAC

TINTED LIP CONDITIONER SPF 15

15 ML/0.5 US FL OZ.

DISTR. BY MAKEUP ART COSMETICS
TORONTO, ONTARIO, CANADA, M5V 1R7